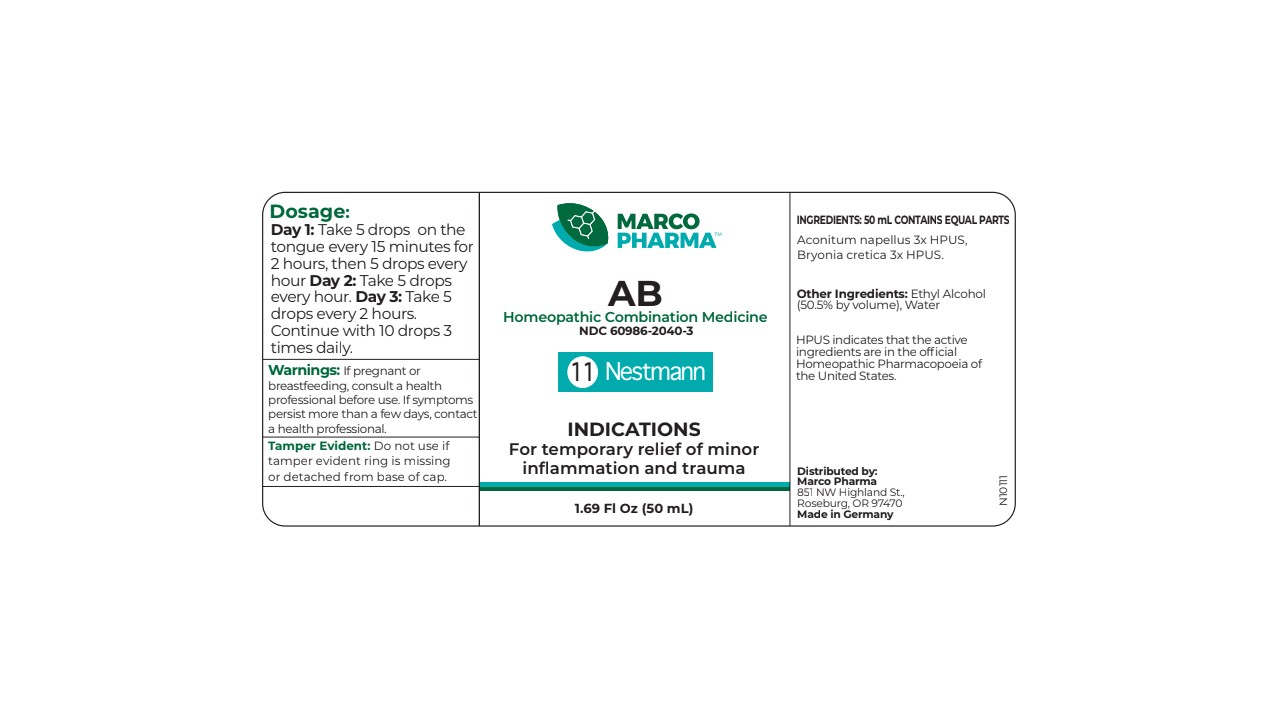 DRUG LABEL: AB
NDC: 60986-2040 | Form: LIQUID
Manufacturer: MARCO PHARMA INTERNATIONAL LLC
Category: homeopathic | Type: HUMAN OTC DRUG LABEL
Date: 20260112

ACTIVE INGREDIENTS: ACONITUM NAPELLUS 3 [hp_X]/100 mL; BRYONIA CRETICA SUBSP. DIOICA ROOT 3 [hp_X]/100 mL
INACTIVE INGREDIENTS: WATER; ALCOHOL

ACTIVE INGREDIENT

ACONITUM NAPELLUS 3X HPUS

BRYONIA CRETICA 3X HPUS

INACTIVE INGREDIENT

ETHYL ALCOHOL 20% V/V

WATER

PURPOSE

FOR TEMPORARY RELIEF OF MINOR INFLAMMATION AND TRAUMA

KEEP OUT OF REACH OF CHILDREN

PREGNANCY OR BREAST FEEDING

IF PREGNANT OR BREAST-FEEDING, CONSULT A HEALTH PROFESSIONAL BEFORE USE

WARNINGS

IF SYMPTOMS PERSIST MORE THAN A FEW DAYS, CONTACT LICENSED PRACTIONER.

INDICATIONS AND USAGE

FOR TEMPORARY RELIEF OF MINOR INFLAMMATION AND TRAUMA

DOSAGE AND ADMINISTRATION

DAY 1; TAKE 5 DROPS ON THE TONGUE EVERY 15 MINUTES FOR 2 HOURS. THEN TAKE 5 DROPS ONCE EVERY HOUR. DAY 2; TAKE 5 DROPS ONCE EVERY HOUR. DAY 3; TAKE 5 DROPS EVERY TWO HOURS. CONTINUE WITH 10 DROPS THREE TIMES DAILY